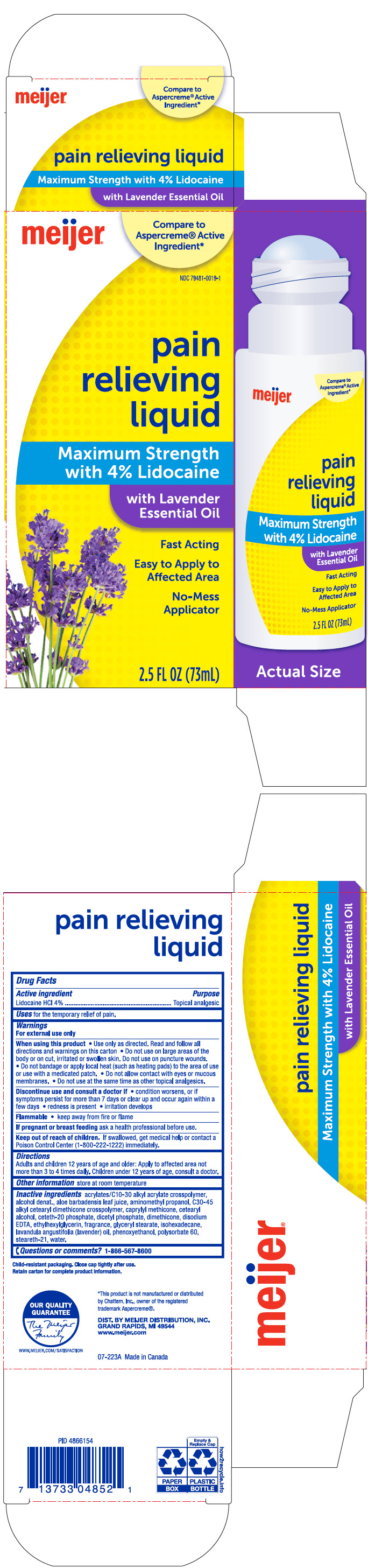 DRUG LABEL: Meijer Pain Relieving Max Strength with Lavender Essential Oil
NDC: 79481-0019 | Form: LIQUID
Manufacturer: Meijer Distribution, Inc
Category: otc | Type: HUMAN OTC DRUG LABEL
Date: 20241115

ACTIVE INGREDIENTS: LIDOCAINE HYDROCHLORIDE 40 mg/1 mL
INACTIVE INGREDIENTS: CARBOMER INTERPOLYMER TYPE A (ALLYL SUCROSE CROSSLINKED); ALCOHOL; ALOE VERA LEAF; AMINOMETHYLPROPANOL; CAPRYLYL TRISILOXANE; CETOSTEARYL ALCOHOL; CETETH-20 PHOSPHATE; DIHEXADECYL PHOSPHATE; Dimethicone; EDETATE DISODIUM; Ethylhexylglycerin; GLYCERYL MONOSTEARATE; Isohexadecane; LAVENDER OIL; Phenoxyethanol; Polysorbate 60; Steareth-21; Water

Meijer® Pain Relieving Liquid Max Strength with Lavender Essential Oil
Topical Analgesic

Drug Facts

Active ingredient

Lidocaine HCl 4%

Purpose

Topical analgesic

Uses

for the temporary relief of pain.

Warnings

For external use only

When using this product

- Use only as directed. Read and follow all directions and warnings on this carton
- Do not use on large areas of the body or on cut, irritated or swollen skin. Do not use on puncture wounds.
- Do not bandage or apply local heat (such as heating pads) to the area of use or use with a medicated patch.
- Do not allow contact with eyes or mucous membranes.
- Do not use at the same time as other topical analgesics.

Discontinue use and consult a doctor if

- condition worsens, or if symptoms persist for more than 7 days or clear up and occur again within a few days
- redness is present
- irritation develops

Flammable

- keep away from fire or flame

PREGNANCY OR BREAST FEEDING

If pregnant or breast feeding ask a health professional before use.

Keep out of reach of children. If swallowed, get medical help or contact a Poison Control Center (1-800-222-1222) immediately.

Directions

Adults and children 12 years of age and older: apply to affected area not more than 3 to 4 times daily. Children under 12 years of age, consult a doctor.

Other information

store at room temperature

Inactive ingredients

acrylates/C10-30 alkyl acrylate crosspolymer, alcohol denat., aloe barbadensis leaf juice, aminomethyl propanol, C30-45 alkyl cetearyl dimethicone crosspolymer, caprylyl methicone, cetearyl alcohol, ceteth-20 phosphate, dicetyl phosphate, dimethicone, disodium EDTA, ethylhexylglycerin, fragrance, glyceryl stearate, isohexadecane, lavandula angustifolia (lavender) oil, phenoxyethanol, polysorbate 60, steareth-21, water.

Questions or comments?

1-866-567-8600

DIST. BY MEIJER DISTRIBUTION, INC.
GRAND RAPIDS, MI 49544

PRINCIPAL DISPLAY PANEL - 73 mL Cylinder Carton

meijer®

Compare to
Aspercreme® Active
Ingredient*

NDC 79481-0019-1

pain
relieving
liquid

Maximum Strength
with 4% Lidocaine

with Lavender
Essential Oil

Fast Acting

Easy to Apply to
Affected Area

No-Mess
Applicator

2.5 FL OZ (73mL)